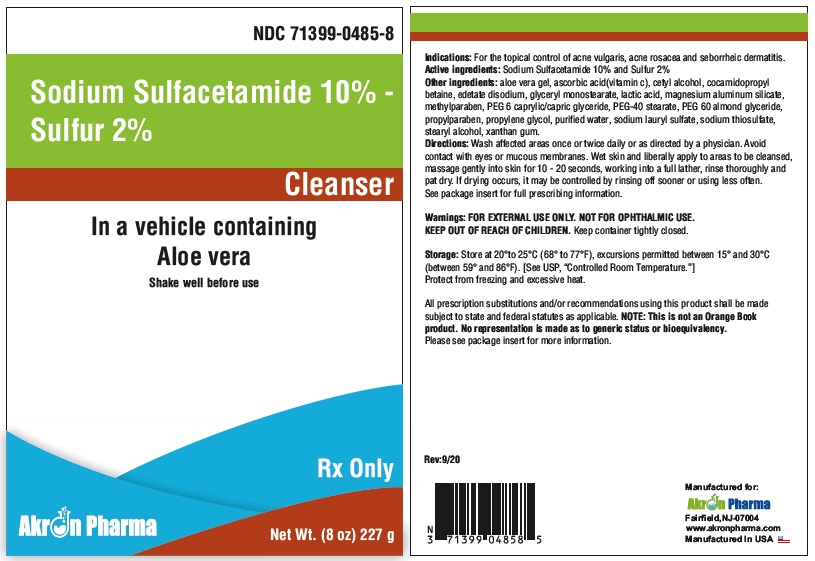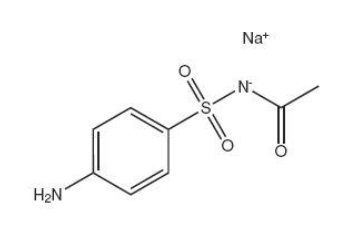 DRUG LABEL: Sodium Sulfacetamide 10% and Sulfur 2% Cleanser
NDC: 71399-0485 | Form: LIQUID
Manufacturer: Akron Pharma Inc.
Category: prescription | Type: HUMAN PRESCRIPTION DRUG LABEL
Date: 20240924

ACTIVE INGREDIENTS: SULFACETAMIDE SODIUM 100 mg/1 g; SULFUR 20 mg/1 g
INACTIVE INGREDIENTS: ALOE VERA LEAF; ASCORBIC ACID; COCAMIDOPROPYL BETAINE; CETYL ALCOHOL; EDETATE DISODIUM; GLYCERYL MONOSTEARATE; LACTIC ACID; MAGNESIUM ALUMINUM SILICATE; METHYLPARABEN; PEG-40 STEARATE; PEG-6 CAPRYLIC/CAPRIC GLYCERIDES; PEG-60 ALMOND GLYCERIDES; PROPYLPARABEN; PROPYLENE GLYCOL; WATER; SODIUM THIOSULFATE; SODIUM LAURYL SULFATE; STEARYL ALCOHOL; XANTHAN GUM

Sodium Sulfacetamide 10% - Sulfur 2% Cleanser

Rx Only

DESCRIPTION

Each gram of SODIUM SULFACETAMIDE 10% - SULFUR 2% CLEANSER (sodium sulfacetamide 10% w/w and sulfur 2% w/w) contains 100 mg of sodium sulfacetamide and 20 mg of colloidal sulfur in a mild aqueous based cleansing vehicle containing aloe vera gel, Ascorbic acid,cocamidopropyl betaine, cetyl alcohol, disodium edetate, glyceryl monostearate, lactic acid, magnesium aluminum silicate, methylparaben, PEG-40 stearate, PEG -6 caprylic/capric glyceride,PEG-60 almond glyceride, propylparaben, propylene glycol,purified water, sodium thiosulfate, sodium lauryl sulfate, stearyl alcohol, and xanthan gum.

Sodium sulfacetamide is a sulfonamide with antibacterial activity while sulfur acts as a keratolytic agent. Sodium sulfacetamide is C8H9N2NaO 3S·H2O with molecular weight of 254.24. Chemically, it is N-[(4-aminophenyl)sulfonyl]-acetamide, monosodium salt, monohydrate.

The structural formula is:

CLINICAL PHARMACOLOGY

The most widely accepted mechanism of action of sulfonamides is the Woods-Fildes theory, which is based on the fact that sulfonamides act as competitive antagonists to para-aminobenzoic acid (PABA), an essential component for bacterial growth. While absorption through intact skin has not been determined, sodium sulfacetamide is readily absorbed from the gastrointestinal tract when taken orally and excreted in the urine, largely unchanged. The biological half-life has variously been reported as 7 to 12.8 hours.
The exact mode of action of sulfur in the treatment of acne is unknown, but it has been reported that it inhibits the growth of Propionibacterium acnes and the formation of free fatty acids.

INDICATIONS

SODIUM SULFACETAMIDE 10% - SULFUR 2% CLEANSER is indicated for use in the topical control of acne vulgaris, acne rosacea and seborrheic dermatitis.

CONTRAINDICATIONS:

SODIUM SULFACETAMIDE 10% - SULFUR 2% CLEANSER is contraindicated for use by patients having known hypersensitivity to sulfonamides, sulfur or any other component of this preparation. SODIUM SULFACETAMIDE 10% - SULFUR 2% CLEANSER is not to be used by patients with kidney disease.

WARNINGS

Although rare, sensitivity to sodium sulfacetamide may occur. Therefore, caution and careful supervision should be observed when prescribing this drug for patients who may be prone to hypersensitivity to topical sulfonamides. Systemic toxic reactions such as agranulocytosis, acute hemolytic anemia, purpura hemorrhagica, drug fever, jaundice and contact dermatitis indicate hypersensitivity to sulfonamides. Particular caution should be employed if areas of denuded or abraded skin are involved.
Sulfonamides are known to cause Stevens-Johnson syndrome in hypersensitive individuals. Stevens-Johnson syndrome also has been reported following the use of sodium sulfacetamide topically. Cases of drug induced systemic lupus erythematosus from topical sulfacetamide also have been reported. In one of these cases, there was a fatal outcome. KEEP OUT OF REACH OF CHILDREN.

PRECAUTIONS

FOR EXTERNAL USE ONLY. NOT FOR OPHTHALMIC USE.
General: If irritation develops, use of the product should be discontinued and appropriate therapy instituted. Patients should be carefully observed for possible local irritation or sensitization during long-term therapy. The object of this therapy is to achieve desquamation without irritation, but sodium sulfacetamide and sulfur can cause reddening and scaling of the epidermis. These side effects are not unusual in the treatment of acne vulgaris, but patients should be cautioned about the possibility.
Carcinogenesis, Mutagenesis and Impairment of Fertility: Long-term studies in animals have not been performed to evaluate carcinogenic potential.
Pregnancy: Category C. Animal reproduction studies have not been conducted with SODIUM SULFACETAMIDE 10% - SULFUR 2% CLEANSER. It is also not known whether SODIUM SULFACETAMIDE 10% - SULFUR 2% CLEANSER can cause fetal harm when administered to a pregnant woman or can affect reproduction capacity. SODIUM SULFACETAMIDE 10% - SULFUR 2% CLEANSER should be given to a pregnant woman only if clearly needed.
Nursing Mothers: It is not known whether sodium sulfacetamide is excreted in human milk following topicaI use of SODIUM SULFACETAMIDE 10% - SULFUR 2% CLEANSER. However, small amounts of orally administered sulfonamides have been reported to be excreted in human milk. In view of this and because many drugs are excreted in human milk, caution should be exercised when SODIUM SULFACETAMIDE 10% - SULFUR 2% CLEANSER is administered to a nursing woman.
Pediatric Use: Safety and effectiveness in children under the age of 12 has not been established.

ADVERSE REACTIONS

Although rare, sodium sulfacetamide may cause local irritation. Call your doctor for medical advice about side effects.

DOSAGE AND ADMINISTRATION

Wash affected areas with SODIUM SULFACETAMIDE 10% - SULFUR 2% CLEANSER 1 to 2 times daily or as directed by a physician. Avoid contact with eyes or mucous membranes. Wet skin and liberally apply to areas to be cleansed, massage gently into skin for 10 to 20 seconds working into a full lather, rinse thoroughly and pat dry. If drying occurs, it may be controlled by rinsing cleanser off sooner or using cleanser less often.

HOW SUPPLIED

SODIUM SULFACETAMIDE 10% - SULFUR 2% CLEANSER is supplied in an 8 oz. (227 g) bottle, NDC 71399-0485-8.

STORAGE

Store at 25°C (77°F); excursions permitted to 15° to 30°C (59° to 86°F). [See USP “Controlled Room Temperature.”]

Note: Protect from freezing and excessive heat. The product may tend to darken slightly on storage. Slight discoloration does not impair the efficacy or safety of the product. Keep container or packet tightly closed.

Occasionally, a slight yellowish discoloration may occur when an excessive amount of the product is used and comes in contact with white fabrics. This discoloration, however, presents no problem, as it is readily removed by ordinary laundering without bleaches.
All prescription substitutions and/or recommendations using this product shall be made subject to state and federal statutes as applicable.

Please NOTE: This is not an Orange Book product and has not been subjected to FDA therapeutic or other equivalency testing. No representation is made as to generic status or bioequivalency. Each person recommending a prescription substitution using this product shall make such recommendation based on his/her professional knowledge and opinion, upon evaluating the active ingredients, inactive ingredients, excipients and chemical information provided herein.

QUESTIONS?
Please Call 1(877) 225-6999

Manufactured for:

Akron Pharma, Inc.

Fairfield, NJ 07004

Manufactured in U.S.A